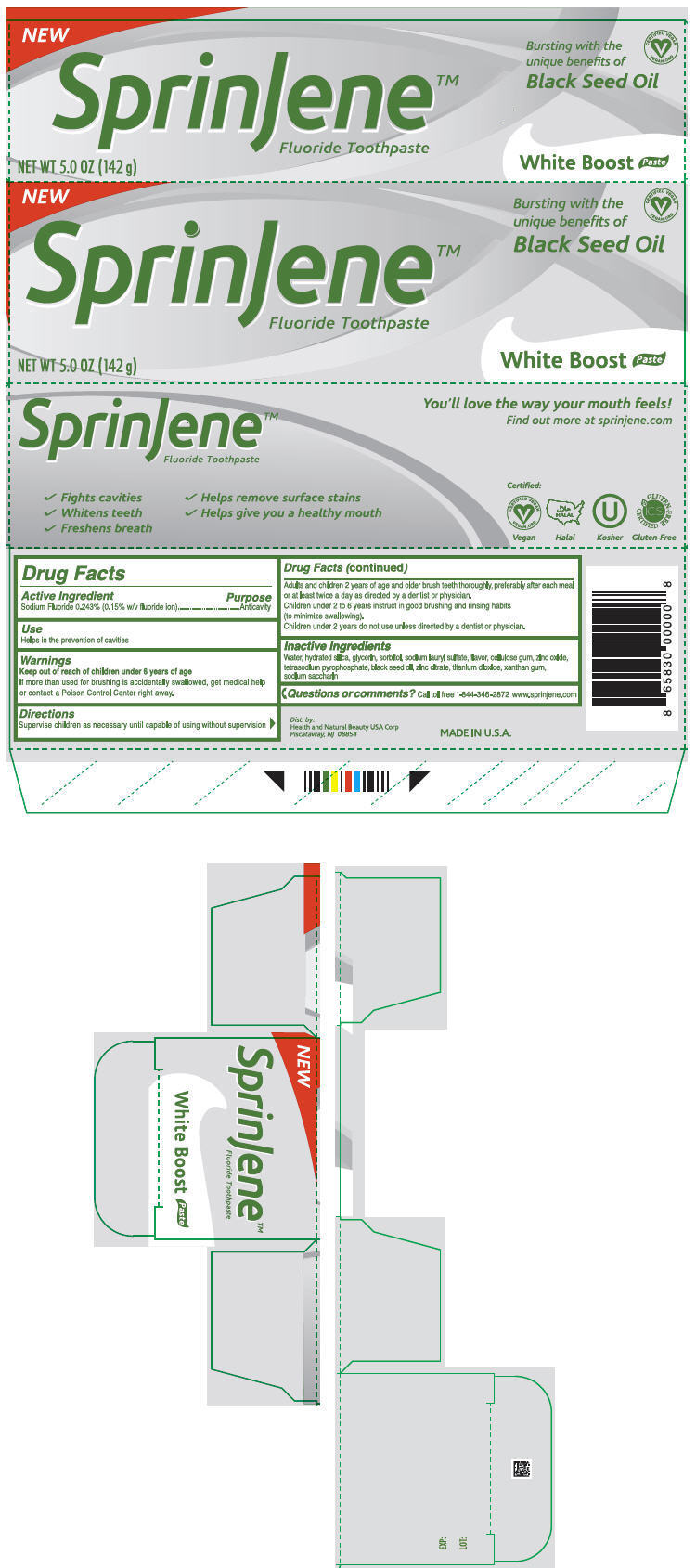 DRUG LABEL: SprinJene 
NDC: 63404-1116 | Form: PASTE, DENTIFRICE
Manufacturer: Health and Natural Beauty USA Corp
Category: otc | Type: HUMAN OTC DRUG LABEL
Date: 20150209

ACTIVE INGREDIENTS: Sodium Fluoride 1.5 mg/1 g
INACTIVE INGREDIENTS: Water; Hydrated Silica; Glycerin; Sorbitol; Sodium Lauryl Sulfate; Carboxymethylcellulose Sodium; Zinc Oxide; Guizotia Abyssinica Seed Oil; Sodium Pyrophosphate; Titanium Dioxide; Zinc Citrate; Xanthan Gum; Saccharin Sodium

SprinJene™
White Boost

Drug Facts

Active Ingredient

Sodium Fluoride 0.243% (0.15% w/v fluoride ion)

Purpose

Anticavity

Use

Helps in the prevention of caries

Warnings

Keep out of reach of children under 6 years of age

If more than used for brushing is accidentally swallowed, get medical help or contact a Poison Control Center right away.

Directions

Supervise children as necessary until capable of using without supervision

Adults and children 2 years of age and older brush teeth thoroughly, preferably after each meal or at least twice a day as directed by a dentist or physician.

Children under 2 to 6 years instruct in good brushing and rinsing habbits (to minimize swallowing).

Children under 2 years do not use unless directed by a dentist or physician.

Inactive Ingredients

Water, hydrated silica, glycerin, sorbitol, sodium lauryl sulfate, flavor, cellulose gum, zinc oxide, tetrasodium pyrophosphate, black seed oil, zinc citrate, titanium dioxide, xanthan gum, sodium saccharin

Questions or comments?

Call toll free 1-844-3-462872
www.sprinjene.com

Dist. by:
Health and Natural Beauty USA Corp
Piscataway, NJ 08854

PRINCIPAL DISPLAY PANEL - 142 g Tube Carton

NEW

SprinJene™
Fluoride Toothpaste

NET WT 5.0 OZ (142 g)

Bursting with the
unique benefits of
Black Seed Oil

CERTIFIED VEGAN
VEGAN.ORG

White Boost Paste